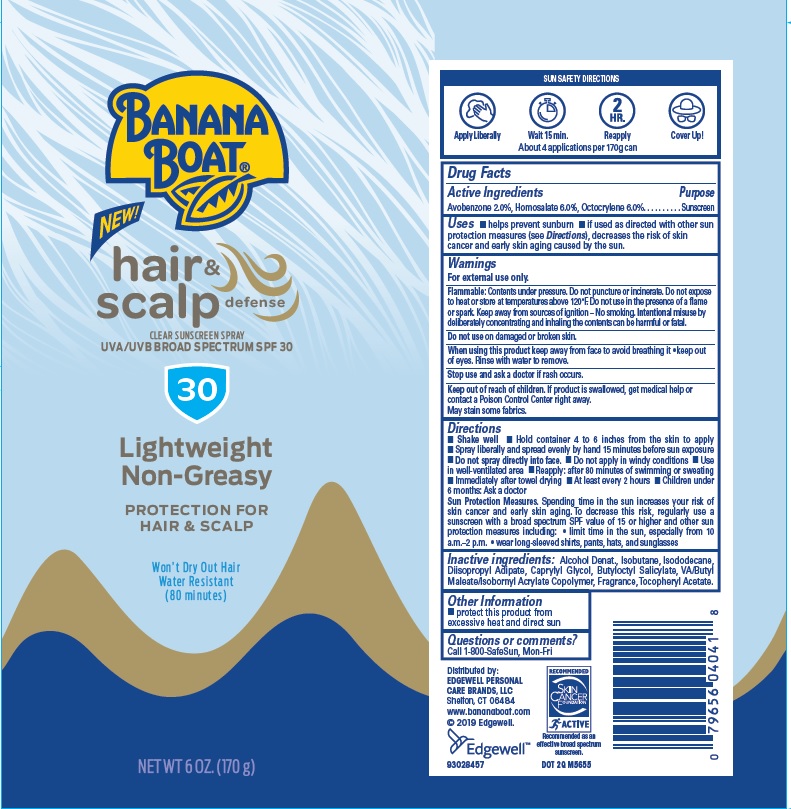 DRUG LABEL: Banana Boat
NDC: 63354-379 | Form: SPRAY
Manufacturer: Edgewell Personal Care Brands LLC
Category: otc | Type: HUMAN OTC DRUG LABEL
Date: 20241027

ACTIVE INGREDIENTS: HOMOSALATE 6 g/100 g; OCTOCRYLENE 6 g/100 g; AVOBENZONE 2 g/100 g
INACTIVE INGREDIENTS: ISOBUTANE; .ALPHA.-TOCOPHEROL ACETATE; CAPRYLYL GLYCOL; BUTYLOCTYL SALICYLATE; ALCOHOL; ISODODECANE; DIISOPROPYL ADIPATE

Active Ingredient

Avobenzone 2.0%, Homosalate 6.0%, Octocrylene 6.0%

Purpose

Sunscreen

Uses

Helps prevent sunburn.

If used as directed with other sun protection measures (see Directions), decreases the risk of skin cancer and early skin aging caused by the sun.

Warnings

For external use only

Flammable

Contents under pressure. Do not puncture or incinerate. Do not expose to heat or store at temperatures above 120°F. Do not use in the presence of a flame or spark. Keep away from sources of ignition - No smoking. Intentional misuse by deliberately concentrating and inhaling the contents can be harmful or fatal.

Do not use

on damaged or broken skin

When using this product

Keep away from face to avoid breathing it. Keep out of eyes. Rinse with water to remove.

Stop use and ask a doctor

if rash occurs.

Keep out of reach of children

If product is swallowed, get medical help or contact a Poison Control Center right away.

May stain

some fabrics.

Directions

• Shake well • Hold container 4 to 6 inches from the skin to apply • Spray liberally and spread evenly by hand 15 minutes before sun exposure • Do not spray directly into face. • Do not apply in windy conditions • Use in well-ventilated area • Reapply: after 80 minutes of swimming or sweating • Immediately after towel drying • At least every 2 hours • Children under 6 months: Ask a doctor
Sun Protection Measures. Spending time in the sun increases your risk of skin cancer and early skin aging. To decrease this risk, regularly use a sunscreen with a broad spectrum SPF value of 15 or higher and other sun protection measures including: • limit time in the sun, especially from 10 a.m. - 2 p.m. • wear long-sleeved shirts,pants, hats, and sunglasses

Inactive Ingredients

Alcohol Denat., Isobutane, Isododecane, Diisopropyl Adipate, Caprylyl Glycol, Butyloctyl Salicylate, VA/Butyl Maleate/Isobornyl Acrylate Copolymer, Fragrance, Tocopheryl Acetate

Other Information

Protect this product from excessive heat and direct sun.

Questions or Comments?

Call 1-800-SafeSun, Mon-Fri

Principal Display Panel

BANANA BOAT®

NEW!

hair & scalp defense

CLEAN SUNSCREEN SPRAY

UVA/UVB BROAD SPECTRUM SPF 30

30

Lightweight

Non-Greasy

PROTECTION FOR HAIR & SCALP

Won't Dry Out Hair

Water Resistant

(80 minutes)

NET WT 6 OZ. (170 g)